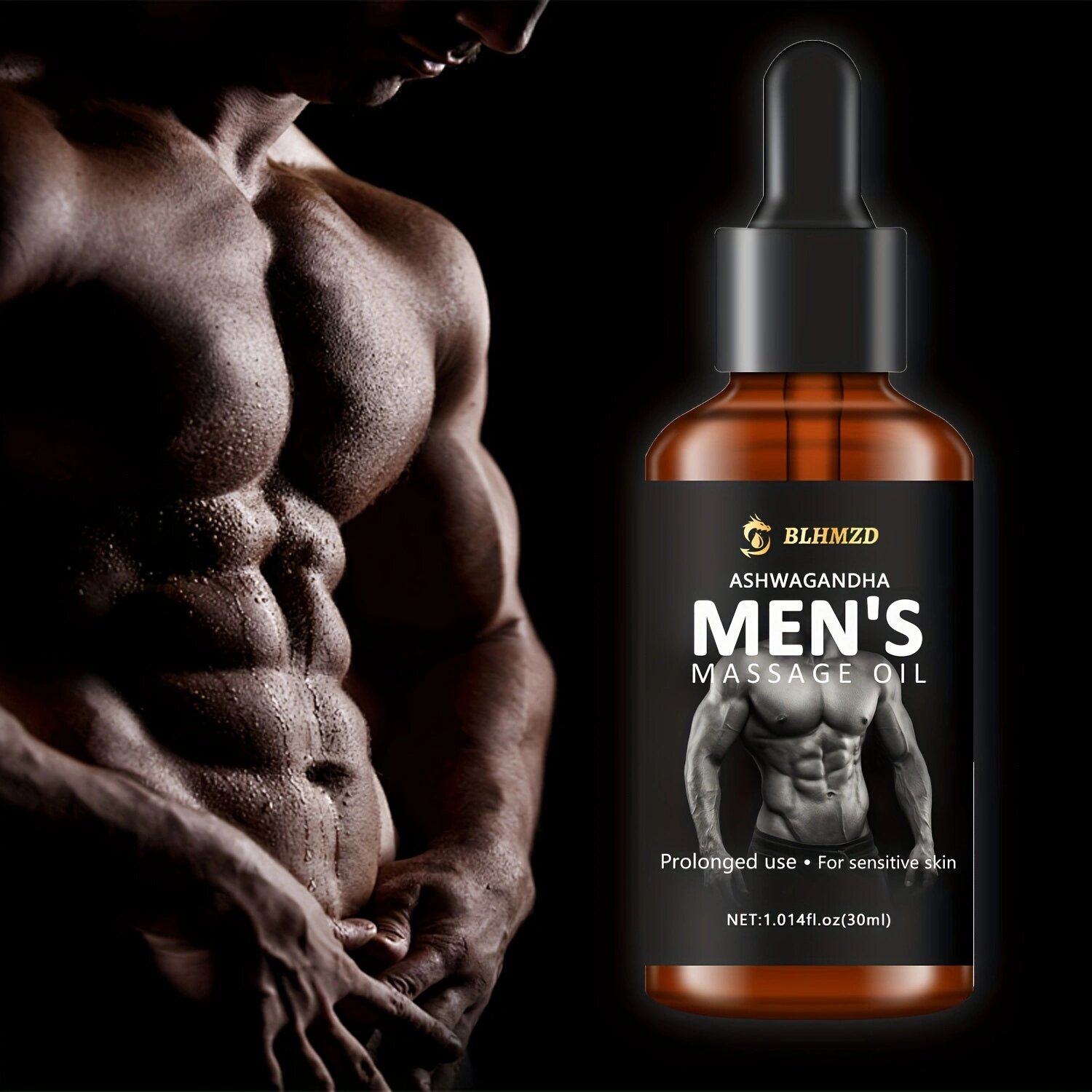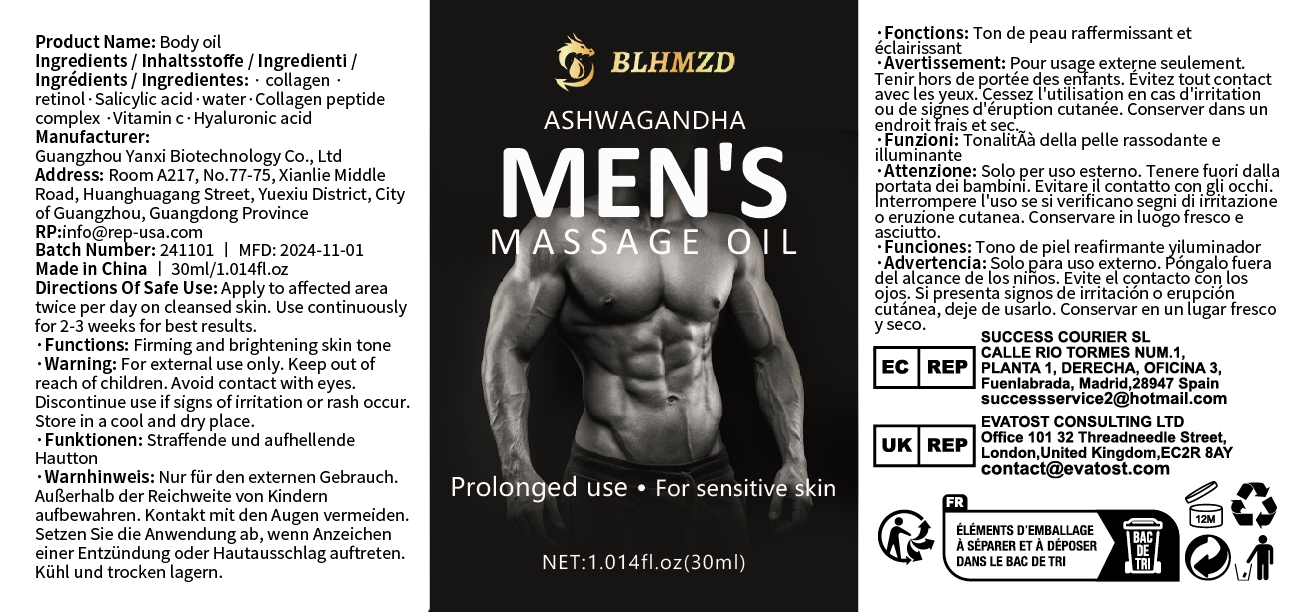 DRUG LABEL: Body oil
NDC: 84025-318 | Form: OIL
Manufacturer: Guangzhou Yanxi Biotechnology Co., Ltd
Category: otc | Type: HUMAN OTC DRUG LABEL
Date: 20250107

ACTIVE INGREDIENTS: RETINOL 5 mg/100 mL; HYALURONIC ACID 3 mg/100 mL
INACTIVE INGREDIENTS: WATER

DOSAGE AND ADMINISTRATION

Apply to affected areatwice per day on cleansed skin. Use continuously for 2-3 weeks for best results.

WARNINGS

keep out of children

INACTIVE INGREDIENT

Aqua

INDICATIONS AND USAGE

for body care

keep out of children

PURPOSE

Moisturize and hydrate the skin